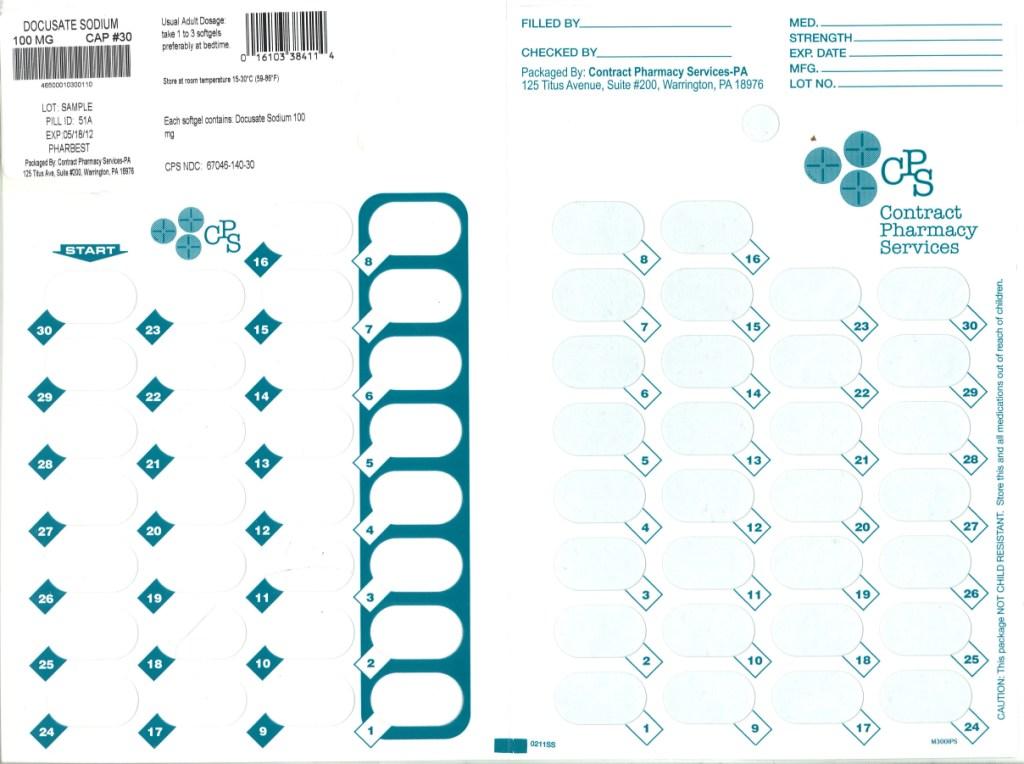 DRUG LABEL: Docusate Sodium
NDC: 67046-140 | Form: CAPSULE
Manufacturer: Contract Pharmacy Services-PA
Category: otc | Type: HUMAN OTC DRUG LABEL
Date: 20180422

ACTIVE INGREDIENTS: DOCUSATE SODIUM 100 mg/1 1
INACTIVE INGREDIENTS: D&C YELLOW NO. 10; FD&C RED NO. 40; GELATIN; GLYCERIN; POLYETHYLENE GLYCOL; PROPYLENE GLYCOL; SORBITOL

Drug Facts

Active ingredient (in each softgel)

Docusate sodium 100 mg

Purpose

Stool softener

Uses

- prevents/relieves dry hard stool
- results usually occurs 1 to 3 days after the first dose

Warnings

Do not use

- when abdominal pain, nausea, or vomiting are present
- for more than one week unless directed by a doctor

Ask a doctor before use if you

- are taking mineral oil
- have noticed a sudden change in bowel habits that last over 2 weeks

Stop use and ask a doctor if

- you have no bowel movement after 3 days
- you have rectal bleeding

These could be signs of a serious condition

If pregnant or breast-feeding,

ask a health professional before use.

Keep out of reach of children.

In case of overdose, get medical help or contact a Poison Control Center right away.

Directions

- do not exceed recommended dose

adults and children over 12 years | take 1-2 softgels daily until first bowel movement; 1 softgel daily thereafter
children 6 to 12 years | take 1 softgel daily
children under 6 years | consult a doctor

Other information

- Tamper Evident: Do not use if safety seal under cap is broken or missing
- store at room temperature 15o to 30oC (59o to 86oF)
- protect from moisture

Questions?

Adverse drug event call: (866) 562-2756